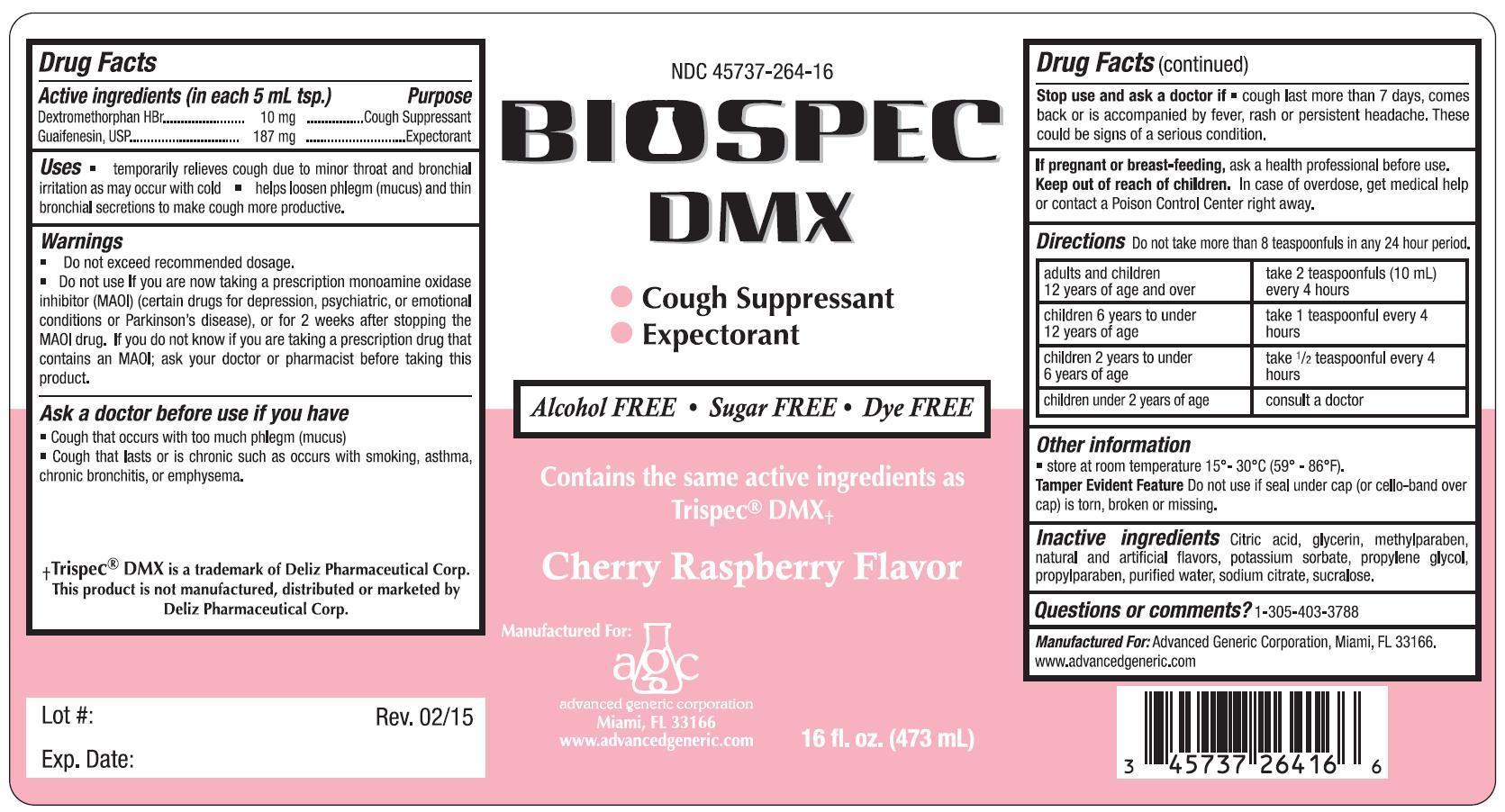 DRUG LABEL: Biospec
NDC: 45737-264 | Form: LIQUID
Manufacturer: Advanced Generic Corporation
Category: otc | Type: HUMAN OTC DRUG LABEL
Date: 20241220

ACTIVE INGREDIENTS: DEXTROMETHORPHAN HYDROBROMIDE 10 mg/5 mL; GUAIFENESIN 187 mg/5 mL
INACTIVE INGREDIENTS: ANHYDROUS CITRIC ACID; GLYCERIN; METHYLPARABEN; POTASSIUM SORBATE; PROPYLENE GLYCOL; PROPYLPARABEN; WATER; SODIUM CITRATE; SUCRALOSE

AGC-BiospecDMX 264

Active Ingredients: (in each 5 mL tsp.) Purpose
Dextromethorphan HBr 10 mg.................. Cough Suppressant
Guaifenesin 187 mg .............................................. Expectorant

Purpose

cough suppressant

expectorant

Uses

temporarily relieves cough due to minor throat and bronchial irritation as may occur with cold

helps loosen phlegm (mucus) and thin bronchial secretions to make cough more productive

Warnings

- Do not exceed recommended dosage.

- Do not use If you are now taking a prescription monoamine oxidase inhibitor (MAOI) (certain drugs for depression, psychiatric, or emotional conditions or Parkinson’s disease), or for 2 weeks after stopping the MAOI drug. If you do not know if you are taking a prescription drug that contains an MAOI; ask your doctor or pharmacist before taking this product.

Ask a doctor before use if you have

- Cough that occurs with too much phlegm (mucus)

- Cough that lasts or is such as occurs with smoking, asthma, chronic bronchitis, or emphysema, or where cough is accompanied by excessive phlegm (mucus) unless directed by a doctor.

Stop use and ask a doctor if

- cough lasts more than 7 days, comes back, or is accompanied by fever, rash or persistent headache. These could be signs of a serious condition.

PREGNANCY OR BREAST FEEDING

If pregnant or breast-feeding,ask a health professional before use.

Keep out of reach of children. In case of overdose, get medical help or contact a Poison Control Center right away.

DOSAGE AND ADMINISTRATION

DirectionsDo not take more than 8 teaspoonfuls in any 24-hour period

adults and children 12 years of age and over | take 2 teaspoonfuls (10 mL) every 4 hours
children 6 years to under 12 years of age | take 1 teaspoonful every 4 hours
children 2 years to under 6 years of age | take 1/2 teaspoonful every 4 hours
children under 2 years of age | consult a doctor

OTHER SAFETY INFORMATION

Other informationstore at room temperature 15-30 C (59-86 F).

Tamper Evident FeatureDo not use if seal under cap (or cello-band over cap) is torn, broken or missing.

INACTIVE INGREDIENT

Inactive ingredients citric acid, glycerin, methylparaben, natural and artificial flavors, potassium sorbate, propylene glycol, propylparaben, purified water, sodium citrate, sucralose

Questions or comments?1-305-403-3788